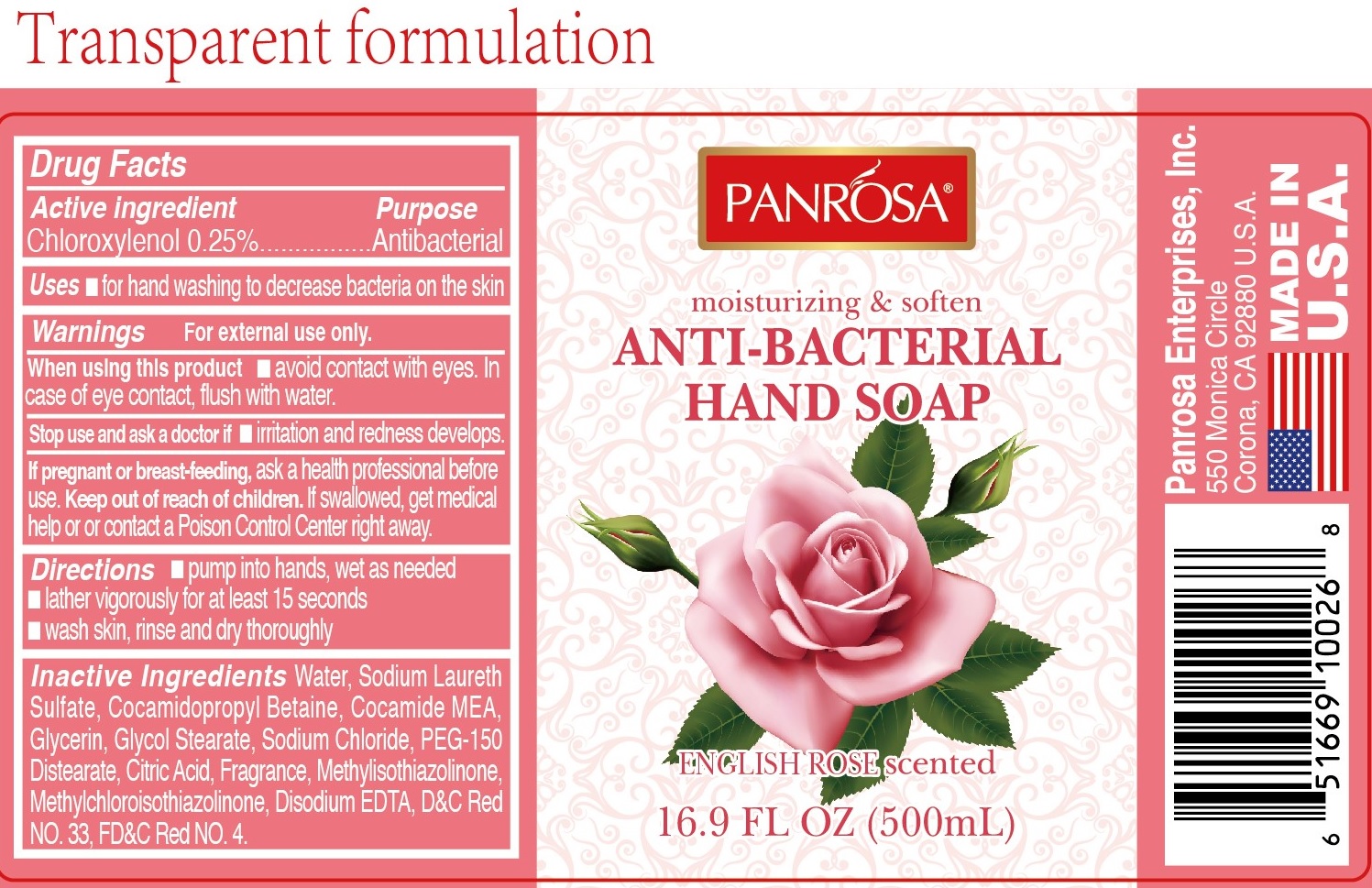 DRUG LABEL: Panrosa Antibacterial Hand Rose
NDC: 50302-016 | Form: GEL
Manufacturer: Panrosa Enterprises, Inc.
Category: otc | Type: HUMAN OTC DRUG LABEL
Date: 20200813

ACTIVE INGREDIENTS: CHLOROXYLENOL 2.5 mg/1 mL
INACTIVE INGREDIENTS: WATER; SODIUM LAURETH SULFATE; COCAMIDOPROPYL BETAINE; COCO MONOETHANOLAMIDE; GLYCERIN; GLYCOL STEARATE; SODIUM CHLORIDE; PEG-150 DISTEARATE; CITRIC ACID MONOHYDRATE; METHYLISOTHIAZOLINONE; METHYLCHLOROISOTHIAZOLINONE; EDETATE DISODIUM ANHYDROUS; D&C RED NO. 33; FD&C RED NO. 4

Panrosa Antibacterial Hand Soap - Rose

Active ingredient

Chloroxylenol 0.25%

Purpose

Antibacterial

Uses

- for hand washing to decrease bacteria on the skin

Warnings

For external use only.

When using this product

- avoid contact with eyes. In case of eye contact, flush with water.

Stop use and ask a doctor if

- irritation and redness develops.

If pregnant or breast-feeding,

ask a health professional before use

Keep out of reach of children.

If swallowed, get medical help or contact a Poison Control Center right away.

Directions

- pump into hands, wet as needed
- lather vigorously for at least 15 seconds
- wash skin, rinse and dry thoroughly

Inactive ingredients

Water, Sodium Laureth Sulfate, Cocamidopropyl Betaine, Cocamide MEA, Glycerin, Glycol Stearate, Sodium Chloride, PEG-150 Distearate, Citric Acid, Fragrance, Methylisothiazolinone, Methylchloroisothiazolinone, Disodium EDTA, D&C Red NO. 33 FD&C Red No.4.